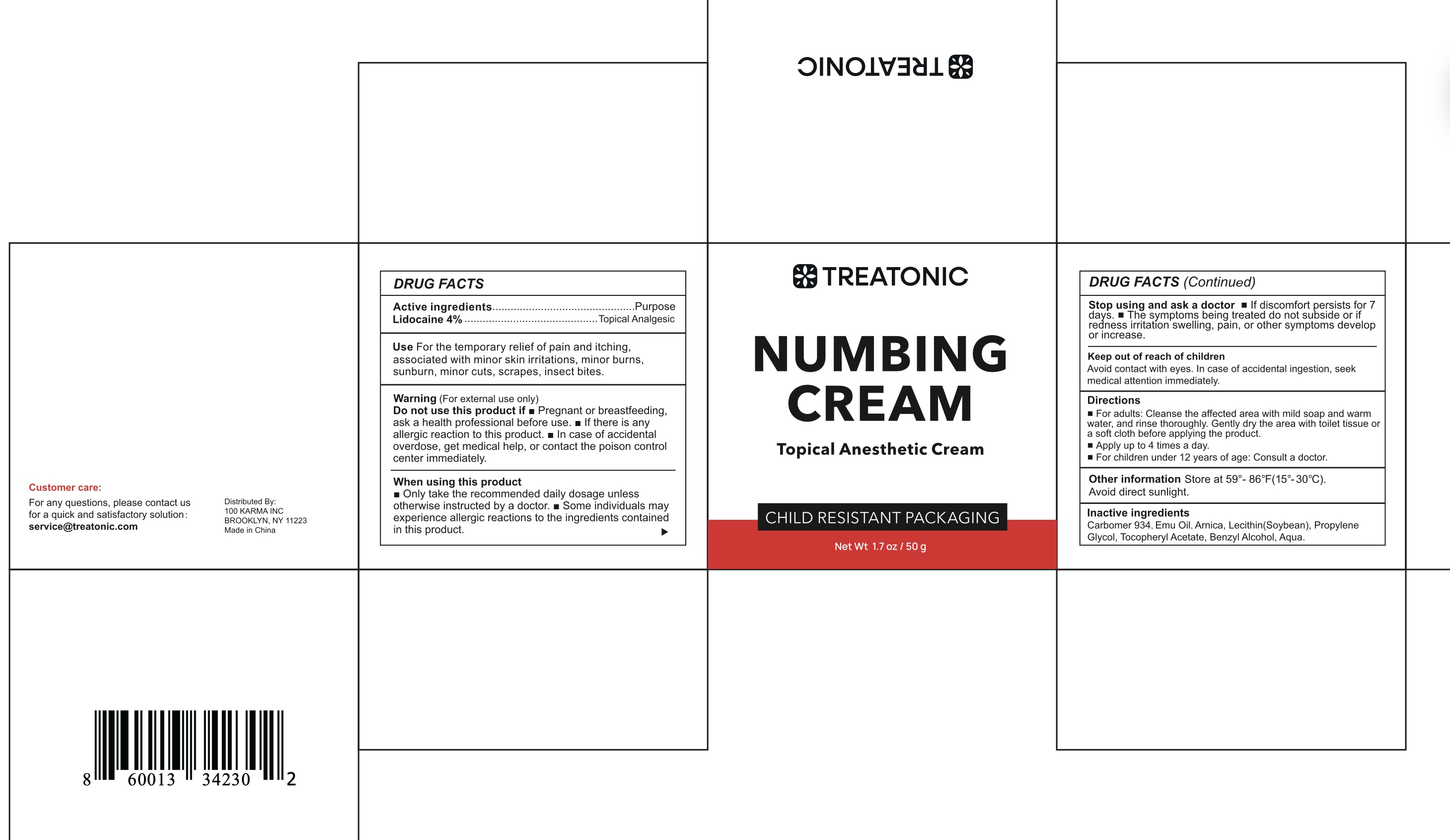 DRUG LABEL: Numbing Cream
NDC: 85569-001 | Form: CREAM
Manufacturer: 100 KARMA INC
Category: otc | Type: HUMAN OTC DRUG LABEL
Date: 20250519

ACTIVE INGREDIENTS: LIDOCAINE 40 mg/1 g
INACTIVE INGREDIENTS: PROPYLENE GLYCOL; BENZYL ALCOHOL; WATER; ARNICA MONTANA FLOWER; EMU OIL; LECITHIN, SOYBEAN; CARBOMER 934; ALPHA-TOCOPHEROL ACETATE

Initial Drug Listing - 4% numbing cream

ACTIVE INGREDIENT

4% lidocaine

PURPOSE

topical analgesic

INDICATIONS AND USAGE

For the temporary relief of pain and itching, associated with minor skin irritations, minor burns, sunburn, minor cuts, scrapes, insect bites.

WARNINGS

For external use only

Do not use this product if

- Pregnant or breastfeeding, ask a health professional before use.
- If there is any allergic reaction to this product.
- In case of accidental overdose, get medical help, or contact the poison control center immediately.

WHEN USING

- Only take the recommended daily dosage unless otherwise instructed by a doctor.
- Some individuals may experience allergic reactions to the ingredients contained in this product.

Stop using and ask a doctor

- If discomfort persists for 7 days.
- The symptoms being treated do not subside or if redness irritation swelling, pain, or other symptoms develop or increase.

Keep out of reach of children Avoid contact with eyes.
In case of accidental ingestion, seek medical attention immediately.

DOSAGE AND ADMINISTRATION

- For adults: Cleanse the affected area with mild soap and warm water, and rinse thoroughly. Gently dry the area with toilet tissue or a soft cloth before applying the product.
- Apply up to 4 times a day.
- For children under 12 years of age: Consult a doctor.

OTHER SAFETY INFORMATION

Store at 59°-86°F (15°-30°C). Avoid direct sunlight.

INACTIVE INGREDIENT

Carbomer 934, Emu Oil, Arnica, Lecithin (Soybean), Propylene Glycol, Tocopheryl Acetate, Benzyl Alcohol, Aqua.